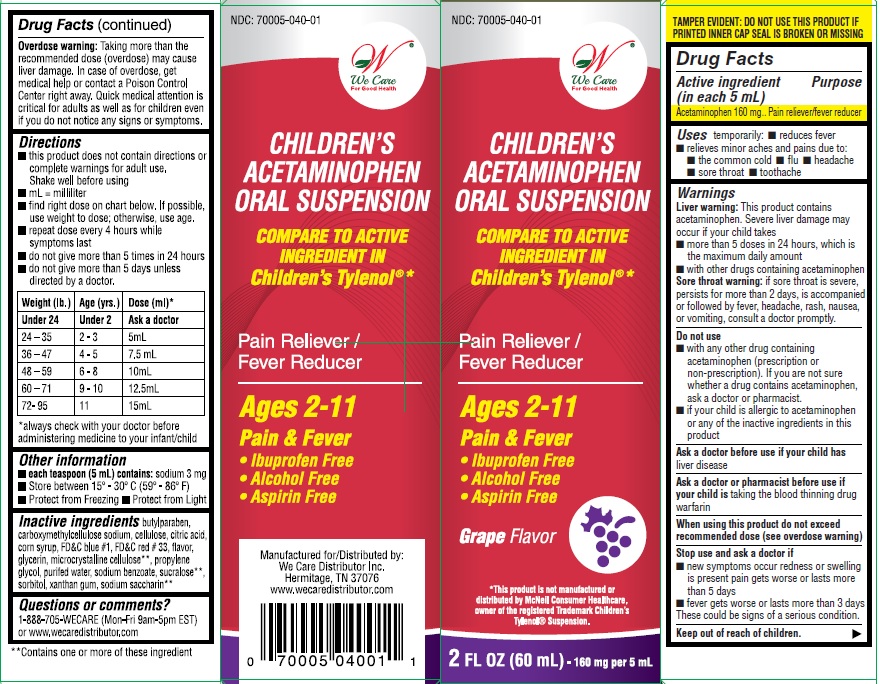 DRUG LABEL: Childrens Acetaminophen Oral Suspension
NDC: 70005-040 | Form: SUSPENSION
Manufacturer: We Care Distributor Inc.
Category: otc | Type: HUMAN OTC DRUG LABEL
Date: 20160926

ACTIVE INGREDIENTS: Acetaminophen 160 mg/5 mL
INACTIVE INGREDIENTS: SODIUM BENZOATE; butylparaben; carboxymethylcellulose sodium; CELLULOSE, MICROCRYSTALLINE; CITRIC ACID MONOHYDRATE; GLYCERIN; HIGH FRUCTOSE CORN SYRUP; PROPYLENE GLYCOL; SORBITOL; SUCRALOSE; XANTHAN GUM; D&C RED NO. 33; FD&C BLUE NO. 1

Drug Facts

Active ingredient

(in each 5 mL)
Acetaminophen 160 mg

Purpose

Acetaminophen
160 mg.............................Pain reliever/fever reducer

Uses

temporarily

- reduces fever
- minor aches and pains due to:
  • the common cold • flu • headache
  • sore throat • toothache

Warnings

Liver warning: This product contains acetaminophen. Severe liver damage may occur if your child takes:
• more than 5 doses in 24 hours, which is the maximum daily amount
• with other drugs containing acetaminophen
Sore throat warning: If sore throat is severe, persists for more than 2 days, is accompanied or followed by fever, headache, rash, nausea, or vomiting, consult a doctor promptly.

Do not use

- with any other drug containing acetaminophen (prescription or non-prescription). If you are not sure whether a drug contains
  acetaminophen, ask a doctor or pharmacist
- if your child is allergic to acetaminophen or any of the inactive ingredients in this product

Ask a doctor before use if your child has

liver disease.

Ask a doctor or pharmacist before use if your child

is taking the blood thinning drug warfarin.

When using this product

do not exceed recommended dose (see overdose warning)

Stop use and ask a doctor if

• new symptoms occur
• redness or swelling is present
• pain gets worse or lasts more than 5 days
• fever gets worse or lasts more than 3 days
These could be signs of a serious condition.

Keep out of reach of children.

Enter section text here

Overdose Warning

Taking more than the recommended dose (overdose) may cause liver damage. In case of overdose, get medical help or contact a Poison Control Center right away. Quick medical attention is critical for adults as well as for children even if you do not notice any signs or symptoms.

Directions

- this product does not contain directions or complete warnings for adult use.
- shake well before using
- mL = mililiter
- find right dose on chart below. If possible, use weight to dose; otherwise, use age.
- repeat dose every 4 hours while symptoms last
- do not give more than 5 times in 24 hours
- do not give more than 5 days unless directed by a doctor

Weight (lb) Age (yr) Dose (tsp or mL)
under 24 under 2 ask a doctor
24-35 2-3 5 mL
36-47 4-5 7.5 mL
48-59 6-8 10 mL
60-71 9-10 12.5 mL
72-95 11 15 mL

always check with your doctor before administering medicine to your infant/child

Other information

- each teaspoon (5mL) contains: sodium 3 mg
- store between 15-30˚C (59-86˚F)
- protect from freezing
- protect from light

Inactive ingredients

butyl paraben, carboxymethylcellulose sodium, cellulose, citric acid, D&C red # 33, FD&C blue # 1, flavors, glycerin, high fructose corn syrup, propylene glycol, purified water, sodium benzoate, sorbitol, sucralose, xanthan gum

QUESTIONS OR COMMENTS?

1-888-705-WECARE (Mon-Fri 9am-5pm EST) or www.wecaredistributor.com

Principal Display Panel

Childrens Acetaminophen Oral Suspension

• Fever reducer
• Pain reliever
Alcohol Free
Aspirin Free
Ibuprofen Free

Grape Flavor

Compare to active ingredient in Childrens Tylenol Fever reducer Pain reliever

2 FL OZ (60 mL)